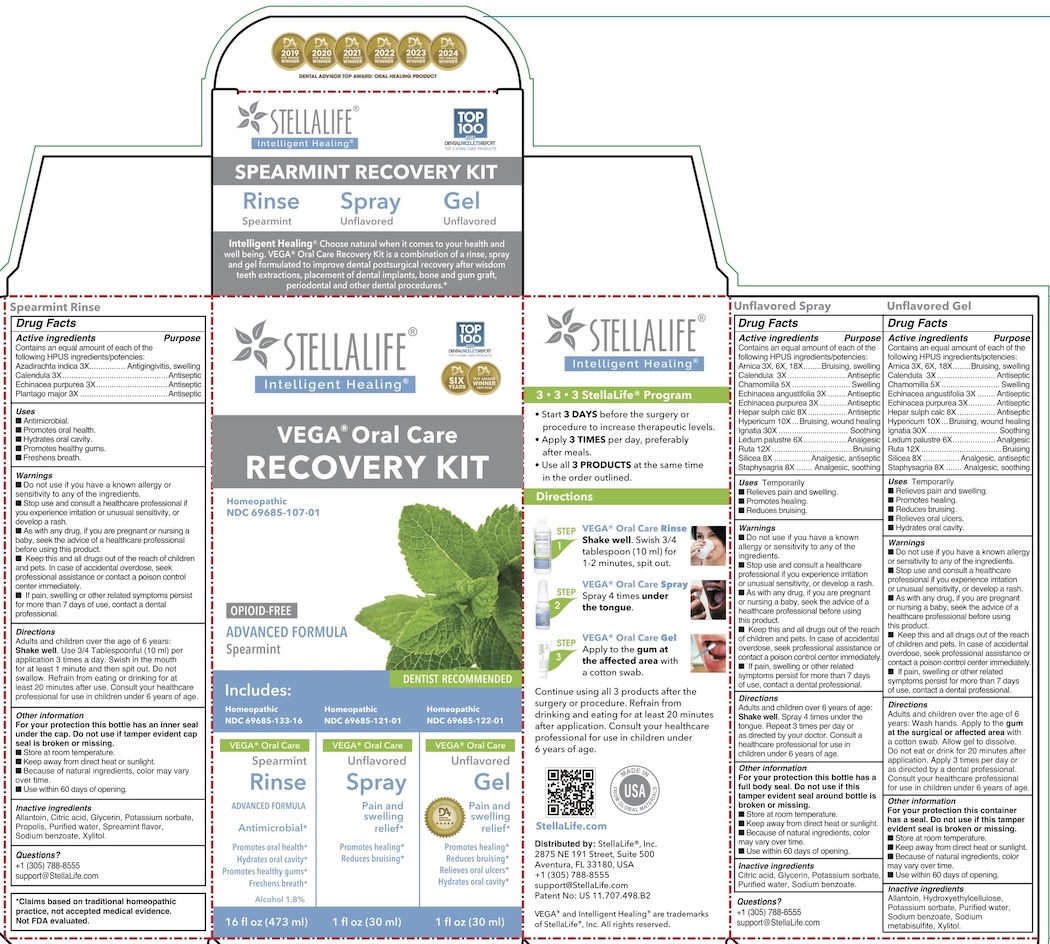 DRUG LABEL: Vega Oral Care Recovery
NDC: 69685-107 | Form: KIT | Route: ORAL
Manufacturer: StellaLife, Inc.
Category: homeopathic | Type: HUMAN OTC DRUG LABEL
Date: 20251222

ACTIVE INGREDIENTS: ECHINACEA PURPUREA 3 [hp_X]/1 mL; PLANTAGO MAJOR 3 [hp_X]/1 mL; CALENDULA OFFICINALIS FLOWER 3 [hp_X]/1 mL; AZADIRACHTA INDICA BARK 3 [hp_X]/1 mL; MATRICARIA RECUTITA 5 [hp_X]/1 mL; SILICON DIOXIDE 8 [hp_X]/1 mL; ECHINACEA ANGUSTIFOLIA 3 [hp_X]/1 mL; ECHINACEA PURPUREA 3 [hp_X]/1 mL; ARNICA MONTANA 3 [hp_X]/1 mL; DELPHINIUM STAPHISAGRIA SEED 8 [hp_X]/1 mL; CALENDULA OFFICINALIS FLOWERING TOP 3 [hp_X]/1 mL; CALCIUM SULFIDE 8 [hp_X]/1 mL; HYPERICUM PERFORATUM 10 [hp_X]/1 mL; LEDUM PALUSTRE TWIG 6 [hp_X]/1 mL; RUTA GRAVEOLENS FLOWERING TOP 12 [hp_X]/1 mL; STRYCHNOS IGNATII SEED 30 [hp_X]/1 mL; MATRICARIA RECUTITA 5 [hp_X]/1 mL; SILICON DIOXIDE 8 [hp_X]/1 mL; ECHINACEA ANGUSTIFOLIA 3 [hp_X]/1 mL; ECHINACEA PURPUREA 3 [hp_X]/1 mL; ARNICA MONTANA 3 [hp_X]/1 mL; DELPHINIUM STAPHISAGRIA SEED 8 [hp_X]/1 mL; CALENDULA OFFICINALIS FLOWERING TOP 3 [hp_X]/1 mL; CALCIUM SULFIDE 8 [hp_X]/1 mL; HYPERICUM PERFORATUM 10 [hp_X]/1 mL; LEDUM PALUSTRE TWIG 6 [hp_X]/1 mL; RUTA GRAVEOLENS FLOWERING TOP 12 [hp_X]/1 mL; STRYCHNOS IGNATII SEED 30 [hp_X]/1 mL
INACTIVE INGREDIENTS: POTASSIUM SORBATE; SODIUM BENZOATE; WATER; ALLANTOIN; PROPOLIS WAX; XYLITOL; ALCOHOL; CITRIC ACID MONOHYDRATE; GLYCERIN; SPEARMINT; GLYCERIN; CITRIC ACID MONOHYDRATE; POTASSIUM SORBATE; SODIUM BENZOATE; WATER; SODIUM METABISULFITE; HYDROXYETHYL CELLULOSE (100 MPA.S AT 2%); POTASSIUM SORBATE; SODIUM BENZOATE; WATER; ALLANTOIN; XYLITOL

Vega Oral Care Recovery Kit - Spearmint

StellaLife VEGA Oral Care Spearmint Rinse

Cucumber Rinse Active Ingredient

Azadirachta indica 3X
Calendula 3X
Echinacea purpurea 3X
Plantago major 3X

Purpose

Active ingredient | Purpose
Azadirachta indica | Antigingivitis, swelling
Calendula | Antiseptic
Echinacea purpurea | Antiseptic
Plantago major | Antiseptic

Uses

■ Antimicrobial.

■ Promotes oral health.

■ Hydrates oral cavity.

■ Supports healthy gums.

■ Freshens breath.

Directions

Adults and children over the age of 6 years: Shake well. Use 3/4 tablespoon (10 ml) per application 3 times a day or as recommended by a dental professional. Swish in the mouth for 1-2 minutes and then spit out. Do not swallow. Refrain from eating or drinking for at least 20 minutes after use. Consult your healthcare professional for use in children under 6 years of age.

Keep out of reach of children

■ Keep this and all drugs out of the reach of children and pets. In case of accidental overdose, seek professional assistance or contact a poison control center immediately.

PREGNANCY AND BREAST FEEDING

■ As with any drug, if you are pregnant or nursing a baby, seek the advice of a healthcare professional before using this product.

Other information

■ Store at room temperature.

■ Keep away from direct heat or sunlight.

■ Because of natural ingredients, color may vary over time.

■ Use within 60 days of opening.

Warnings

For your protection, this bottle has an inner seal under the cap. Do not use if tamper evident cap seal is broken or missing.

Stop use

■ Stop use and consult a healthcare professional if you experience irritation or unusual sensitivity, or develop a rash.

Ask doctor

■ If pain, swelling or other related symptoms persist for more than 7 days of use, contact a dental professional.

INACTIVE INGREDIENT

Alcohol, Allantoin, Citric acid, Cucumber flavor, Glycerin, Potassium sorbate, Propolis, Purified water, Sodium benzoate, Xylitol.

Questions?

(305) 788-8555 or
support@StellaLife.com

Unflavored Spray

Unflavored Spray Active Ingredients

Arnica 3X, 6X, 18X, Calendula 3X, Chamomilla 5X, Echinacea angustifolia 3X, Echinacea purpurea 3X, Hepar sulph calc 8X, Hypericum 10X, lgnatia 30X, Ruta 12X, Silicea 8X, Staphysagria 8X

Unflavored Spray Pregnancy

■ As with any drug, if you are pregnant or nursing a baby, seek the advice of a healthcare professional before using this product.

Purpose

Active Ingredient | Purpose
Arnica | Bruising, swelling
Calendula | Antiseptic
Chamomilla | Swelling
Echinacea angustifolia | Antiseptic
Echinacea purpurea | Antiseptic
Hepar sulph calc | Antiseptic
Hypericum | Bruising, wound healing
lgnatia | Soothing
Ledum palustre | Analgesic
Ruta | Bruising
Silicea | Analgesic, antiseptic
Staphysagria | Analgesic, soothing

Keep out of reach of children

■ Keep this and all drugs out of the reach of children. In case of accidental overdose, seek professional assistance or contact a poison control center immediately.

Warnings

For your protection, this bottle has a full body seal. Do not use if this tamper evident seal is broken or missing.

Directions

Adults and children over 6 years of age: Shake well. Spray 3-4 times per application under the tongue. Repeat 3-4 times per day or as directed by your doctor. Consult a healthcare professional for use in children under 6 years of age.

Unflavored Spray Uses

■ Relieves pain and swelling.

■ Promotes healing.

■ Reducing bruising.

■ Do not use if you have a known allergy or sensitivity to any of the ingredients.

Stop use

■ Stop use and consult a healthcare professional if you experience irritation or unusual sensitivity, or develop a rash.

Ask dental professional

■ If pain, swelling or other related symptoms persist for more than 7 days of use, contact a dental professional.

Other information

■ Store at room temperature.

■ Keep away from direct heat or sunlight.

■ Because of natural ingredients. color may vary overtime.

■ Use within 60 days of opening

Questions?

(305) 788-8555 or

Support@StellaLife.com

Unflavored Gel

Directions

Adults and children over the age of 6 years: Wash hands. Apply to the gum at the surgical or affected area with a cotton swab. Allow gel to dissolve. Do not eat or drink for 20 minutes after application. Apply 4 times per day or as directed by a dental professional. Consult your healthcare professional for use in children under6 years of age.

Keep out of reach of children

■ Keep this and all drugs out of the reach of children and pets. In case of accidental overdose, seek professional assistance or contact a poison control center immediately

Pregnancy

■ As with any drug, if you are pregnant or nursing a baby, seek the advice of a health professional before using this product.

Inactive Ingredients

Allantoin, Hydroxyethylcellulose, Potassium sorbate, Purified water, Sodium benzoate, Sodium metabisulfite, Xylitol.

■ Do not use if you have a known allergy or sensitivity to any of the ingredients.

Stop Use

■ Stop use and consult a health professional is you experience irritation or unusual sensitivity, or develop a rash,

Warnings

For your protection this container has a seal. Do not use if this tamper evident seal is broken or missing.

Ask Dental Professional

■ If pain, swelling or other related symptoms persist for more than7 days of use, contact a dental professional.

Other Information

■ Store at room temperature.

■ Keep away from direct heat or sunlight.

■ Because of natural ingredients. color may vary overtime.

■ Use within 60 days of opening

Questions?

(305) 788-8555 or

support@StellaLife.com

Unflavored Gel Active Ingredients

Arnica 3X, 6X, 18X, Calendula 3X, Chamomilla 5X, Echinacea angustifolia 3X, Echinacea purpurea 3X, Hepar sulph calc 8X, Hypericum 10X, lgnatia 30X, Ruta 12X, Silicea 8X, Staphysagria 8X

Purpose

Active Ingredient | Purpose
Arnica | Bruising, swelling
Calendula | Antiseptic
Chamomilla | Swelling
Echinacea angustifolia | Antiseptic
Echinacea purpurea | Antiseptic
Hepar sulph calc | Antiseptic
Hypericum | Bruising, wound healing
lgnatia | Soothing
Ledum palustre | Analgesic
Ruta | Bruising
Silicea | Analgesic, antiseptic
Staphysagria | Analgesic, soothing

Uses

Temporarily

- Relieves pain and swelling.
- Promotes healing.
- Reduces bruising.
- Relieves oral ulcers.
- Hydrates oral